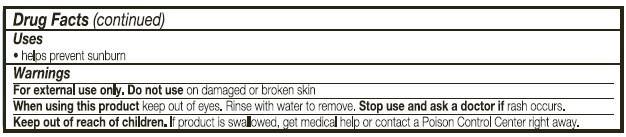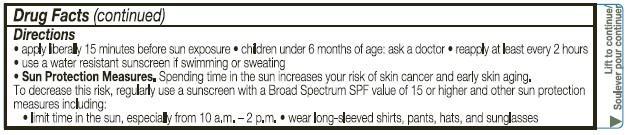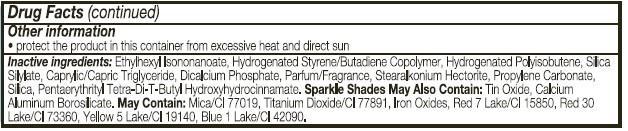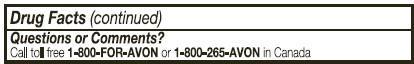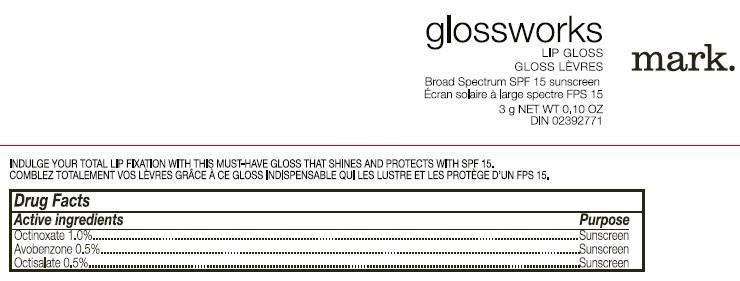 DRUG LABEL: mark
NDC: 10096-0298 | Form: LIPSTICK
Manufacturer: Avon Products, Inc
Category: otc | Type: HUMAN OTC DRUG LABEL
Date: 20130329

ACTIVE INGREDIENTS: OCTINOXATE 10 mg/1 g; AVOBENZONE 5 mg/1 g; OCTISALATE 5 mg/1 g

Active ingredient
Octinoxate 1.0%................................

Avobenzone 0.5%................................

Octisalate 0.5%................................

Purpose
.................................Sunscreen

.................................Sunscreen

.................................Sunscreen

Uses
• helps prevent sunburn

Warnings
For external use only

Do not use on damaged or broken skin

When using this product keep out of eyes. Rinse with water to remove.

Stop use and ask a doctor if rash occurs

Keep out of reach of children. If swallowed, get medical help or contact a Poison Control Center right away.

Directions
• apply liberally 15 minutes before sun exposure
• children under 6 months of age: ask a doctor
• reapply at least every 2 hours
• use a water resistant sunscreen if swimming or sweating
• Sun Protection Measures. Spending time in the sun increases your risk of skin cancer and early skin aging. To decrease this risk, regularly use a sunscreen with a Broad Spectrum SPF value of 15 or higher and other sun protection measures including:
• limit time in the sun, especially from 10 a.m. – 2 p.m.
• wear long-sleeved shirts, pants, hats, and sunglasses

Other information

• protect the product in this container from excessive heat and direct sun

Inactive Ingredients:
ETHYLHEXYL ISONONANOATE, HYDROGENATED STYRENE/BUTADIENE COPOLYMER, HYDROGENATED POLYISOBUTENE, SILICA SILYLATE, CAPRYLIC/CAPRIC TRIGLYCERIDE, DICALCIUM PHOSPHATE, PARFUM/FRAGRANCE, STEARALKONIUM HECTORITE, PROPYLENE CARBONATE,
SILICA, PENTAERYTHRITYL TETRA-DI-T-BUTYL HYDROXYHYDROCINNAMATE SPARKLE SHADES MAY ALSO CONTAIN: TIN OXIDE, CALCIUM ALUMINUM BOROSILICATE MAY CONTAIN: MICA/CI 77019, TITANIUM DIOXIDE/CI 7789, IRON OXIDES, RED 7 LAKE/CI 15850, RED 30 LAKE/CI 73360, YELLOW 5 LAKE/CI 19140, BLUE 1 LAKE/CI 42090

Questions or Comments?
Call toll free 1-800-FOR-AVON or 1-800-265-AVON in Canada